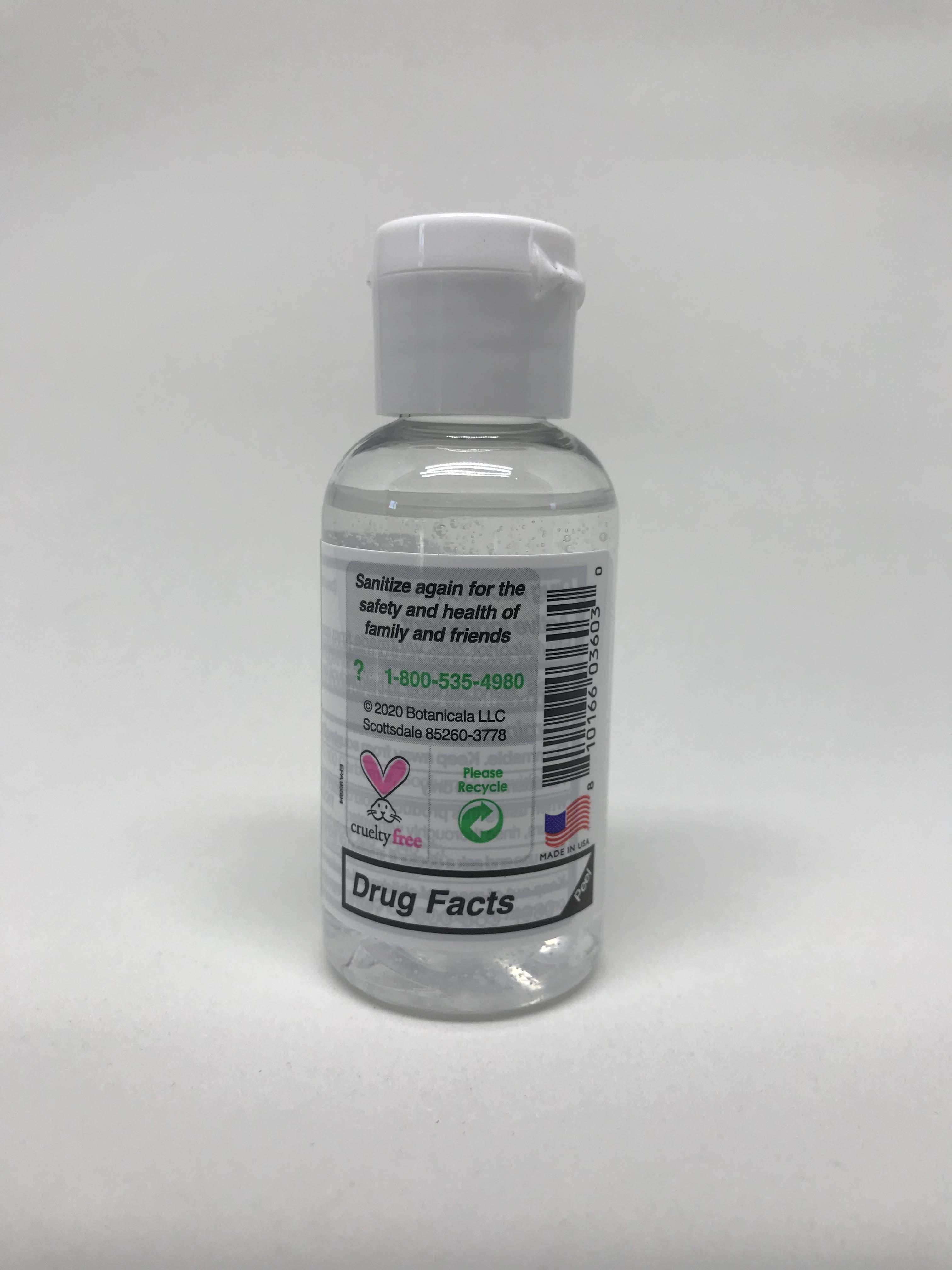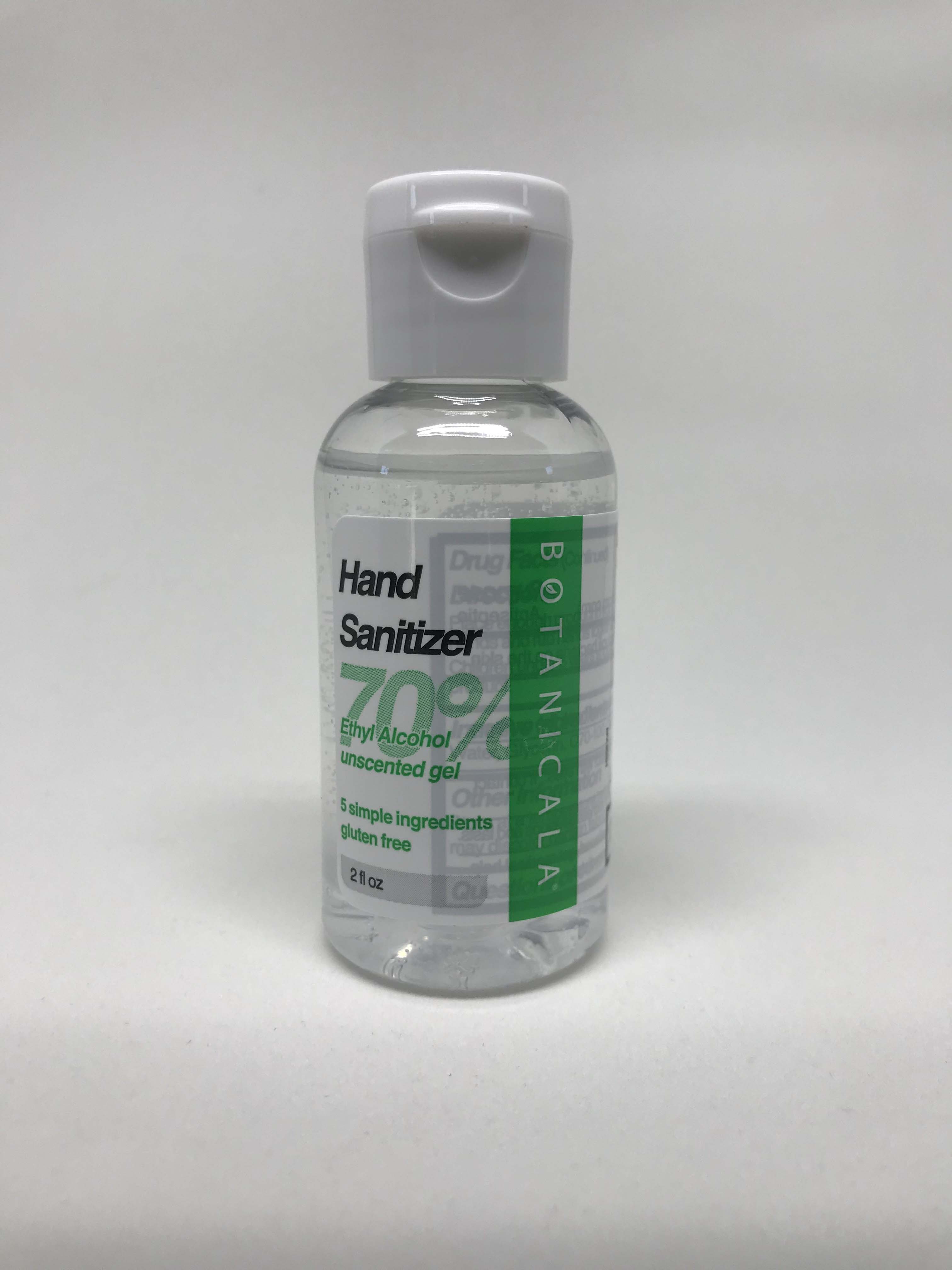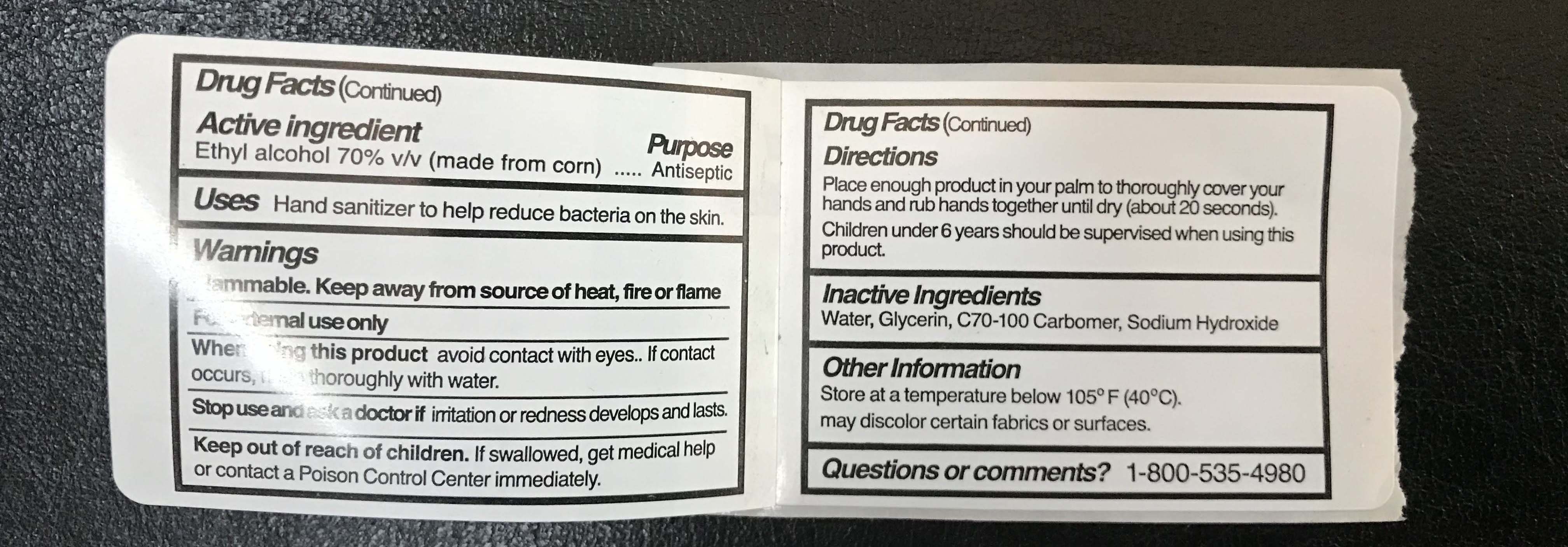 DRUG LABEL: Hand Sanitizer
NDC: 77709-603 | Form: GEL
Manufacturer: Botanicala LLC
Category: otc | Type: HUMAN OTC DRUG LABEL
Date: 20200506

ACTIVE INGREDIENTS: ALCOHOL 70 mL/100 mL
INACTIVE INGREDIENTS: GLYCERIN 2.5 mL/100 mL; CARBOMER 980 0.2 g/100 mL; WATER; SODIUM HYDROXIDE 0.01 g/100 mL

Botanicala 70% Ethyl Alcohol Hand Sanitizer

The hand sanitizer is manufactured using only the following United States Pharmacopoeia (USP) grade ingredients in the preparation of the product (percentage in final product formulation) consistent with Center for Disease Control (CDC) recommendations:

1. Alcohol (ethanol) (USP or Food Chemical Codex (FCC) grade) (70%, volume/volume (v/v)) in an aqueous solution denatured according to Alcohol and Tobacco Tax and Trade Bureau regulations in 27 CFR part 20.
2. Glycerol (2% v/v).
3. Carbomer 980 (0.2% v/v).
4. Sodium Hydroxide (<0.02% v/v).
5. Sterile ultrapure water.

The firm does not add other active or inactive ingredients. Different or additional ingredients may impact the quality and potency of the product.

Active Ingredient(s)

Alcohol 70% v/v. Purpose: Antiseptic

Purpose

Hand Sanitizer to help reduce bacteria on the skin

Use

Hand Sanitizer to help reduce bacteria on the skin

Warnings

Flammable. Keep away from source of heat, fire, or flame. For external use only.

When using this product keep out of eyes, ears, and mouth. In case of contact with eyes, rinse eyes thoroughly with water.

Stop use and ask a doctor if irritation or redness develops and lasts

Keep out of reach of children. If swallowed, get medical help or contact a Poison Control Center immediately

Directions

- Place enough product in your palm to thoroughly cover your hands and rub hands together until dry (about 20 seconds)
- Children under 6 years of age should be supervised when using this product.

Other information

- Store at a temperature below 105F (40C)
- May discolor certain fabrics or surfaces

Inactive ingredients

Water, Glycerin, C70-100 Carbomer, Sodium Hydroxide

Questions or comments? 1-800-535-4980

Package Label - Principal Display Panel

55 mL NDC: 99907-603-01